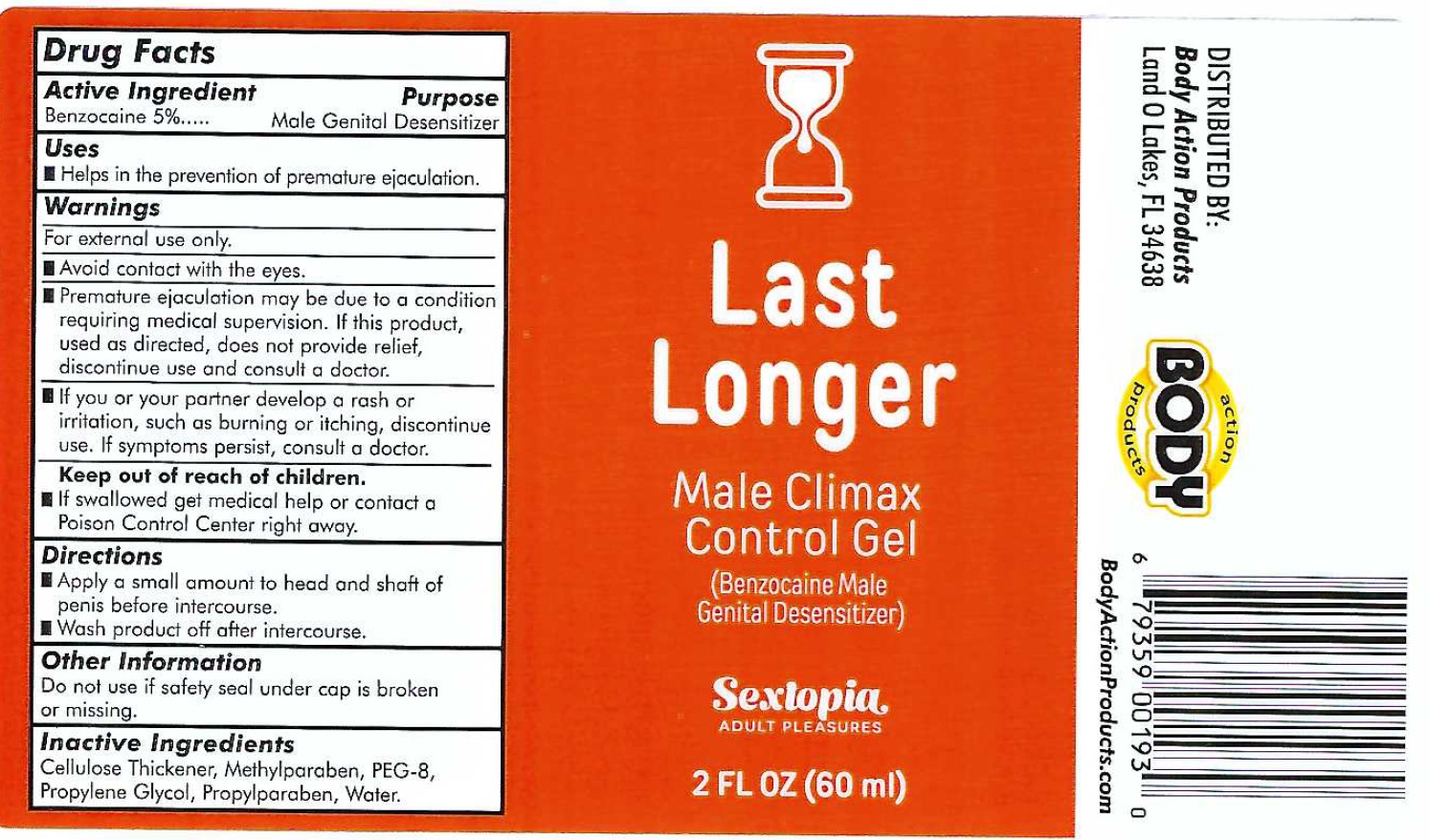 DRUG LABEL: Last Longer Male Climax Control
NDC: 70742-503 | Form: GEL
Manufacturer: PRODUCT MAX GROUP INC
Category: otc | Type: HUMAN OTC DRUG LABEL
Date: 20240612

ACTIVE INGREDIENTS: BENZOCAINE 50 mg/1 mL
INACTIVE INGREDIENTS: METHYLPARABEN; POLYETHYLENE GLYCOL 400; PROPYLENE GLYCOL; PROPYLPARABEN; WATER

Last Longer Male Climax Control Gel

Active Ingredient

Benzocaine 5%

Purpose

Male Genital Desensitizer

Uses

- Helps in the prevention of premature ejaculation.

Warnings

For external use only.

- Avoid contact with the eyes.
- Premature ejaculation may be due to a condition requiring medical supervision. If this product, used as directed, does not provide relief, discontinue use and consult a doctor.
- If you or your partner develop a rash or irritation, such as burning or itching, discontinue use. If symptoms persist, consult a doctor.

Keep out of reach of children.

- If swallowed get medical help or contact a Poison Control Center right away.

Directions

- Apply a small amount to head and shaft of penis before intercourse.
- Wash product off after intercourse.

Other Information

Do not use if safety seal under cap is broken or missing.

Inactive Ingredients

Cellulose Thickener, Methylparaben, PEG-8, Propylene Glycol, Propylparaben, Water.